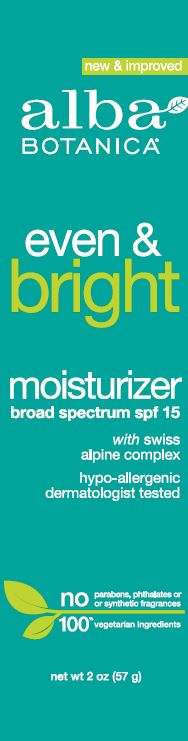 DRUG LABEL: Even and Bright Moisturizer SPF15
NDC: 61995-0312 | Form: LOTION
Manufacturer: The Hain Celestial Group
Category: otc | Type: HUMAN OTC DRUG LABEL
Date: 20221027

ACTIVE INGREDIENTS: OCTISALATE 5 g/100 g; AVOBENZONE 3 g/100 g; OCTOCRYLENE 10 g/100 g
INACTIVE INGREDIENTS: BIOSACCHARIDE GUM-1; GUAR GUM; ERYTHRITOL; LINALYL ACETATE; LECITHIN, SOYBEAN; SODIUM ANISATE; ORANGE OIL; CAESALPINIA SPINOSA RESIN; SODIUM CHLORIDE; SODIUM HYDROXIDE; XANTHAN GUM; MENTHA PIPERITA LEAF; ACHILLEA MILLEFOLIUM FLOWERING TOP; ASCORBYL GLUCOSIDE; MEDIUM-CHAIN TRIGLYCERIDES; ANHYDROUS CITRIC ACID; COCO-CAPRYLATE/CAPRATE; DIACETYL BOLDINE; GLYCERYL CAPRYLATE; HOMARINE HYDROCHLORIDE; PULLULAN; HYDRATED SILICA; SODIUM CITRATE; ETHYLHEXYLGLYCERIN; TRIETHYL CITRATE; LAMINARIA DIGITATA; ULVA LACTUCA; VERONICA OFFICINALIS FLOWERING TOP; ASCORBIC ACID; WATER; COCONUT ALKANES; GLYCERIN; SODIUM STEAROYL GLUTAMATE; ACHILLEA MILLEFOLIUM FLOWER; ALOE VERA LEAF; SODIUM LEVULINATE; ALCOHOL; PHENOXYETHANOL; POTASSIUM SORBATE; SODIUM BENZOATE; .ALPHA.-AMYLCINNAMALDEHYDE; LIMONENE, (+/-)-; COUMARIN; LINALOOL, (+/-)-; CUCUMBER; GLYCYRRHIZA GLABRA; MALVA SYLVESTRIS FLOWER; MELISSA OFFICINALIS LEAF; STARCH, RICE; PRIMULA VERIS; .ALPHA.-TOCOPHEROL ACETATE, DL-

Even & Bright SPF 15

ACTIVE INGREDIENT

Avobenzone 3%

Octisalate 5%

Octocrylene 10%

DOSAGE AND ADMINISTRATION

Apply liberally 15 minutes before sun exposure. Reapply every 2 hours during sun exposure. Use water resistant sunscreen if swimming or sweating. Sun Protection Measures: Spending time in the sun increase risk of skin cancer and early skin aging. To decrease risk, regularly use sunscreen with Broad Spectrum SPF 15 or higherand other preventive measures including:

- Limit time in the sun, especially from 10am to 2pm
- wear long-sleeved shirts, pants and sunglasses

PURPOSE

Sunscreen

WARNINGS

For external use only. Do not use on damaged or broken skin. When using this product, keep out of eyes. Rinse with water to remove. Stop use and ask a doctor if skin rash occurs. If swallowed, get medical help or contact a Poison Control Center right away.

Keep out of reach of children.

INACTIVE INGREDIENT

Water (Aqua), Coconut Alkanes, Glycerin, Sodium Stearoyl Glutamate, Citrus Aurantium Dulcis (Orange) Peel Oil, Shea Butter Ethyl Esters, Achillea Millefolium Flower Extract (1), Achillea Millefolium Flower/Leaf/Stem Extract, Alchemilla Vulgaris Flower/Leaf/Stem Extract, Aloe Barbadensis Leaf Juice (1), Caesalpinia Spinosa Gum, Cucumis Sativus (Cucumber) Fruit Extract, Enteromorpha Compressa Extract, Glycyrrhiza Glabra (Licorice) Root Extract (1), Laminaria Digitata Extract, Malva Sylvestris (Mallow) Flower Extract, Melissa Officinalis Leaf Extract, Mentha Piperita (Peppermint) Leaf Extract, Oryza Sativa (Rice) Starch, Primula Veris Extract, Ulva Lactuca Extract (1), Veronica Officinalis Flower/Leaf/Stem Extract, Ascorbic Acid, Ascorbyl Glucoside, Tocopheryl Acetate, Biosaccharide Gum-1, Caprylic/Capric Triglyceride, Citric Acid, Coco-Caprylate/Caprate, Cyamopsis Tetragonoloba (Guar) Gum (1), Diacetyl Boldine, Erythritol, Glyceryl Caprylate, Homarine HCl, Linalyl Acetate, Lysolecithin, Pullulan, Sclerotium Gum, Silica, Sodium Anisate, Sodium Chloride, Sodium Citrate, Sodium Hydroxide, Sodium Levulinate, Triethyl Citrate, Xanthan Gum, Alcohol, Ethylhexylglycerin, Phenoxyethanol, Potassium Sorbate, Sodium Benzoate, Amyl Cinnamal, Coumarin, Limonene, Linalool

(1) Certified Organic Ingredient

INDICATIONS AND USAGE

Sunscreen